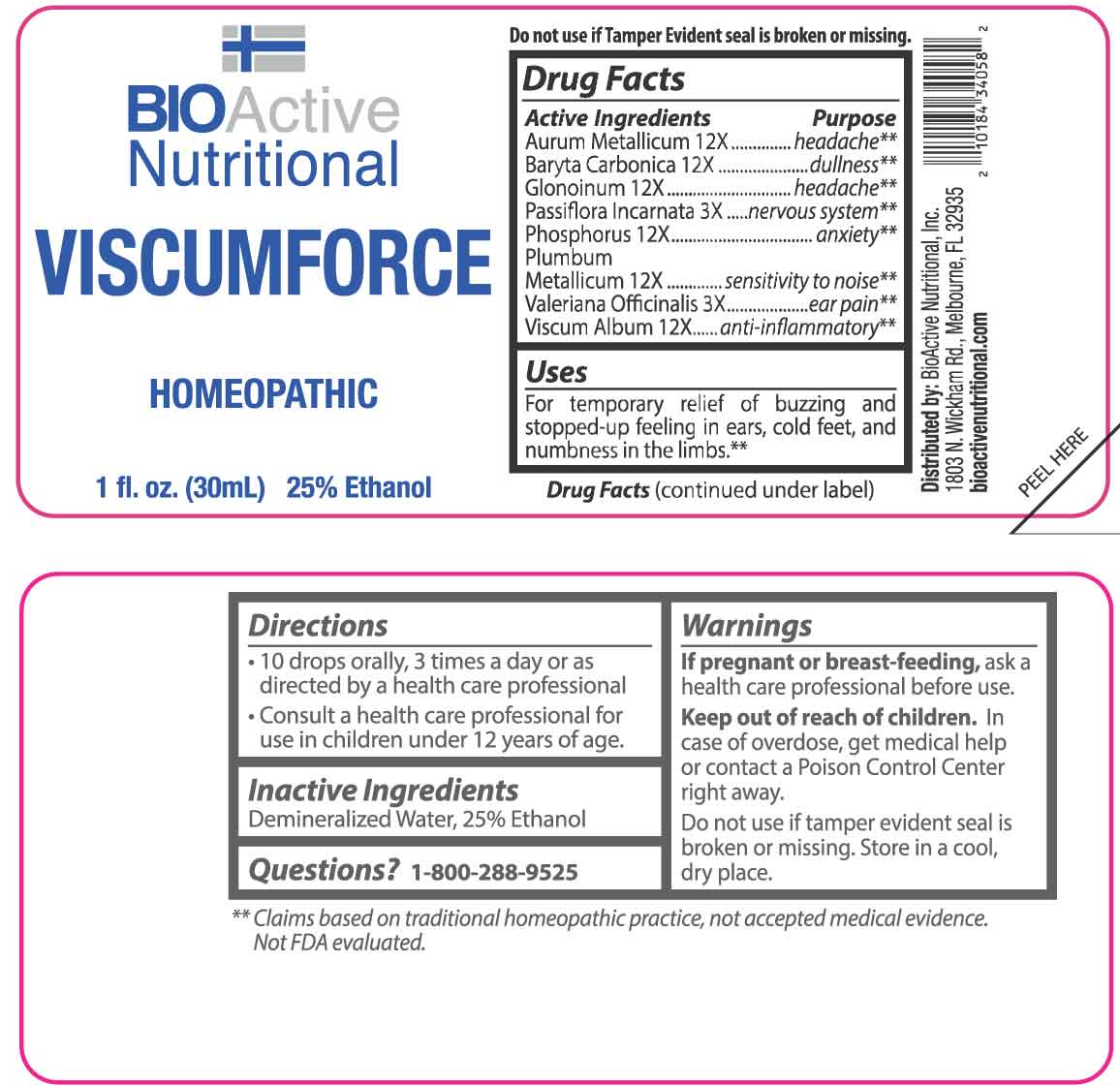 DRUG LABEL: Viscumforce
NDC: 43857-0109 | Form: LIQUID
Manufacturer: BioActive Nutritional, Inc.
Category: homeopathic | Type: HUMAN OTC DRUG LABEL
Date: 20251215

ACTIVE INGREDIENTS: PASSIFLORA INCARNATA FLOWERING TOP 3 [hp_X]/1 mL; VALERIAN 3 [hp_X]/1 mL; GOLD 12 [hp_X]/1 mL; BARIUM CARBONATE 12 [hp_X]/1 mL; NITROGLYCERIN 12 [hp_X]/1 mL; PHOSPHORUS 12 [hp_X]/1 mL; LEAD 12 [hp_X]/1 mL; VISCUM ALBUM FRUITING TOP 12 [hp_X]/1 mL
INACTIVE INGREDIENTS: WATER; ALCOHOL

DRUG FACTS:

ACTIVE INGREDIENTS:

Aurum Metallicum 12X, Baryta Carbonica 12X, Glonoinum 12X, Passiflora Incarnata 3X, Phosphorus 12X, Plumbum Metallicum 12X, Valeriana Officinalis 3X, Viscum Album 12X.

PURPOSE:

Aurum Metallicum - headache,** Baryta Carbonica - dullness,** Glonoinum - headache,** Passiflora Incarnata – nervous system,** Phosphorus - anxiety,** Plumbum Metallicum – sensitivity to noise,** Valeriana Officinalis – ear pain,** Viscum Album – anti-inflammatory**

**Claims based on traditional homeopathic practice, not accepted medical evidence. Not FDA evaluated.

USES:

For temporary relief of buzzing and stopped-up feeling in ears, cold feet, and numbness in the limbs.**

**Claims based on traditional homeopathic practice, not accepted medical evidence. Not FDA evaluated.

WARNINGS:

If pregnant or breast-feeding, ask a health care professional before use.

Keep out of reach of children. In case of overdose, get medical help or contact a Poison Control Center right away.

Do not use if tamper evident seal is broken or missing.

Store in a cool, dry place.

KEEP OUT OF REACH OF CHILDREN:

In case of overdose, get medical help or contact a Poison Control Center right away.

DIRECTIONS:

• 10 drops orally, 3 times a day or as directed by a health care professional.

• Consult a health care professional for use in children under 12 years of age.

INACTIVE INGREDIENTS:

Demineralized Water, 25% Ethanol

QUESTIONS:

Distributed by:
BioActive Nutritional, Inc.
1803 N. Wickham Rd.
Melbourne, FL 32935
bioactivenutritional.com

1-800-288-9525

PACKAGE LABEL DISPLAY:

BIOActive Nutritional

VISCUMFORCE

HOMEOPATHIC

1 fl. oz. (30 mL)